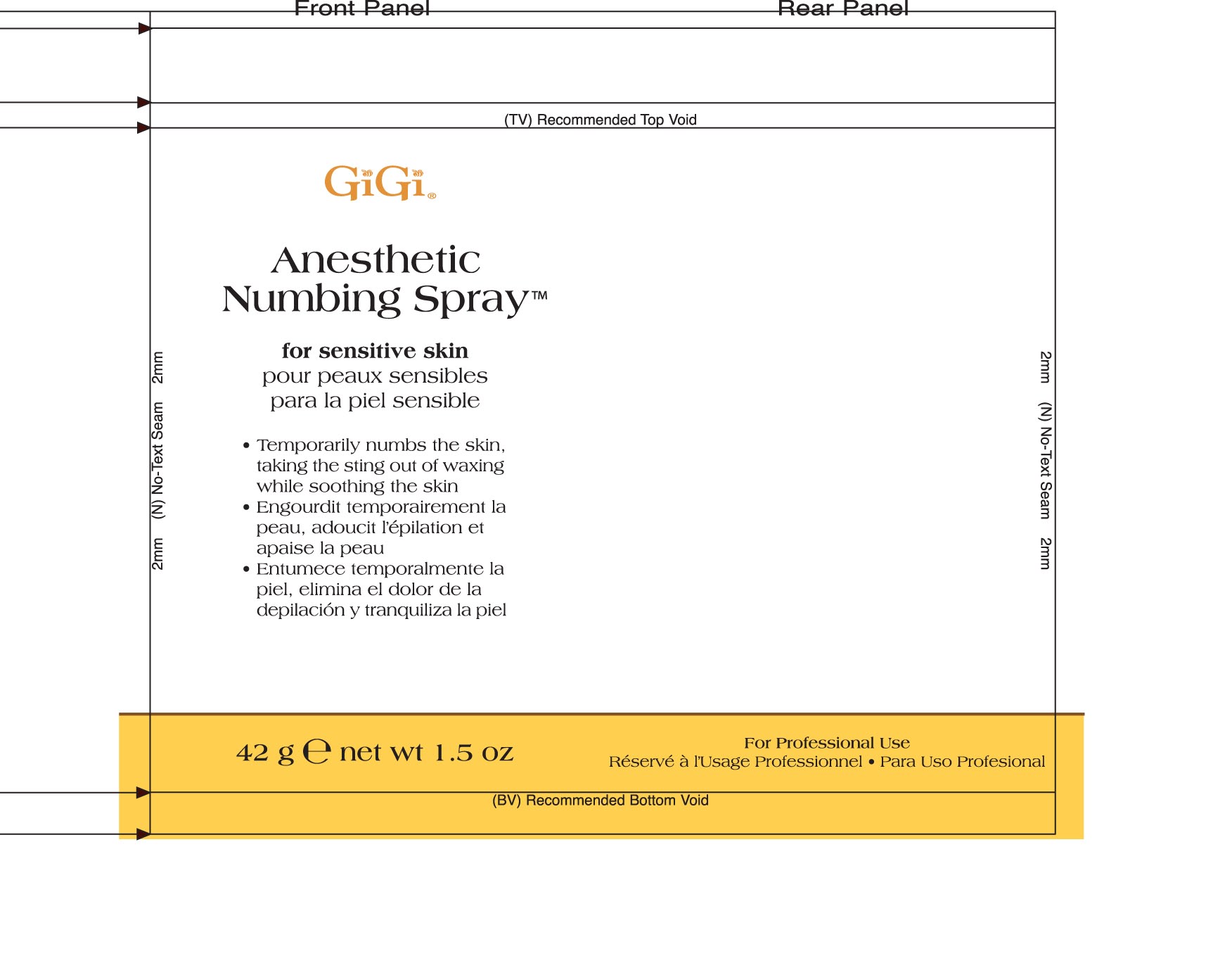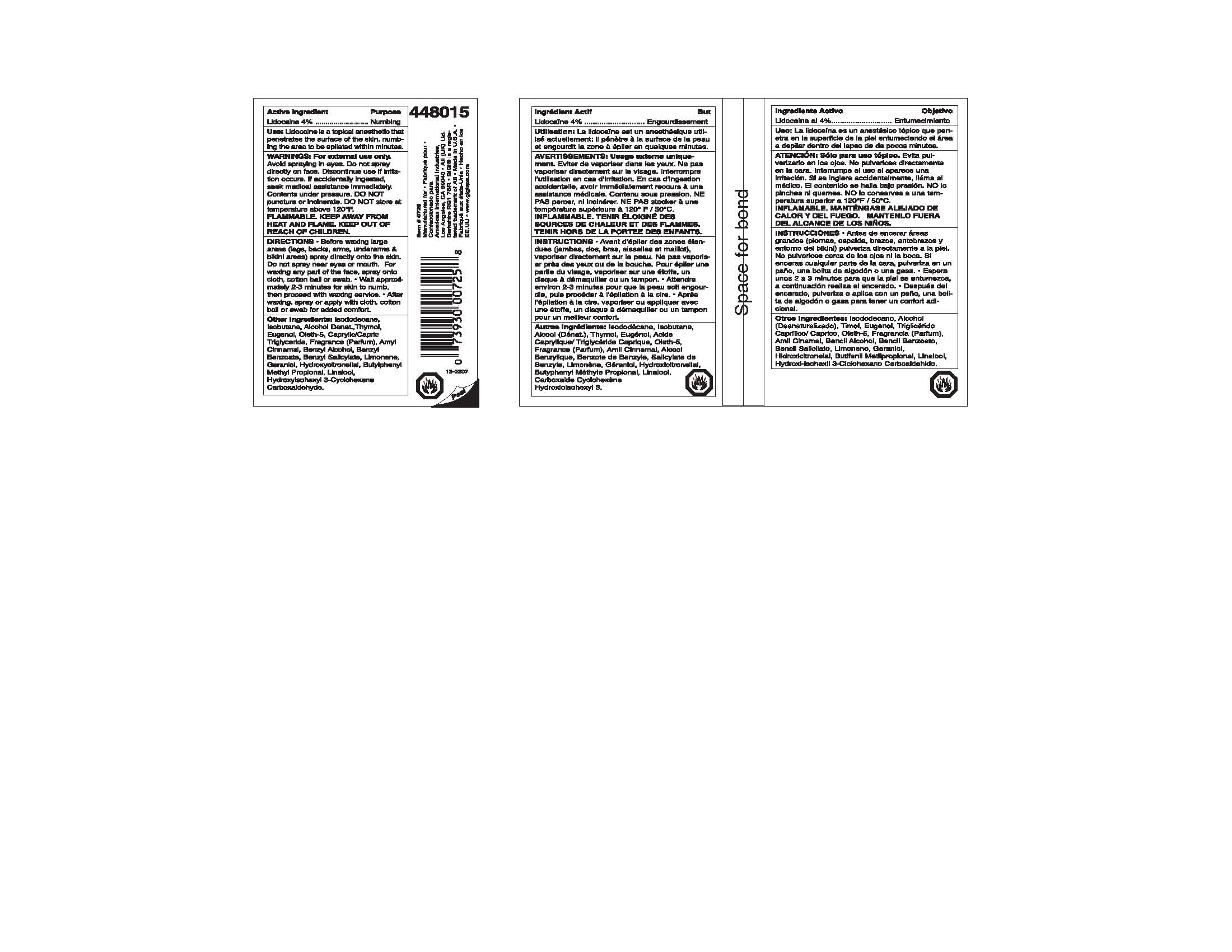 DRUG LABEL: GIGI ANESTHETIC NUMBING
NDC: 57367-001 | Form: AEROSOL
Manufacturer: 220 LABORATORIES INC
Category: otc | Type: HUMAN OTC DRUG LABEL
Date: 20100510

ACTIVE INGREDIENTS: LIDOCAINE 40 mg/1 g
INACTIVE INGREDIENTS: ISOBUTANE; THYMOL; EUGENOL; ALCOHOL; MEDIUM-CHAIN TRIGLYCERIDES; OLETH-5; ISODODECANE

NUMBING SPRAY CONTAINER

ACTIVE INGREDIENT - LIDOCAINE 4%
PURPOSE - NUMBING

PURPOSE

Uses: Lidocaine is a topical anesthetic that penetrates the surface of the skin, numbing the area to be epilated within minutes.

WARNINGS AND PRECAUTIONS

Warnings: For external use only. Avoid spraying in eyes. Do not spray directly on face. Discontinue use if irritation occurs. If accidentally ingested, seek medical assistance immediately. Contents under pressure. Do not puncture or incinerate. Do not store at temperature above 120°F.
FLAMMABLE. KEEP AWAY FROM HEAT AND FLAME. KEEP OUT OF REACH OF CHILDREN.

DOSAGE AND ADMINISTRATION

Directions - Before waxing large areas (legs, backs, arms, underarms and bikini areas) spray directly onto the skin. Do not spray near eyes or mouth. For waxing any part of the face, spray onto cloth, cotton ball or swab. Wait approximately 2-3 minutes for skin to numb, then proceed with waxing service. After waxing, spray or apply with cloth, cotton ball or swab for added comfort.

PACKAGE LABEL

GiGi Anesthetic Numbing Spray
for sensitive skin
Temporarily numbs the skin taking the sting out of waxing while soothing the skin.